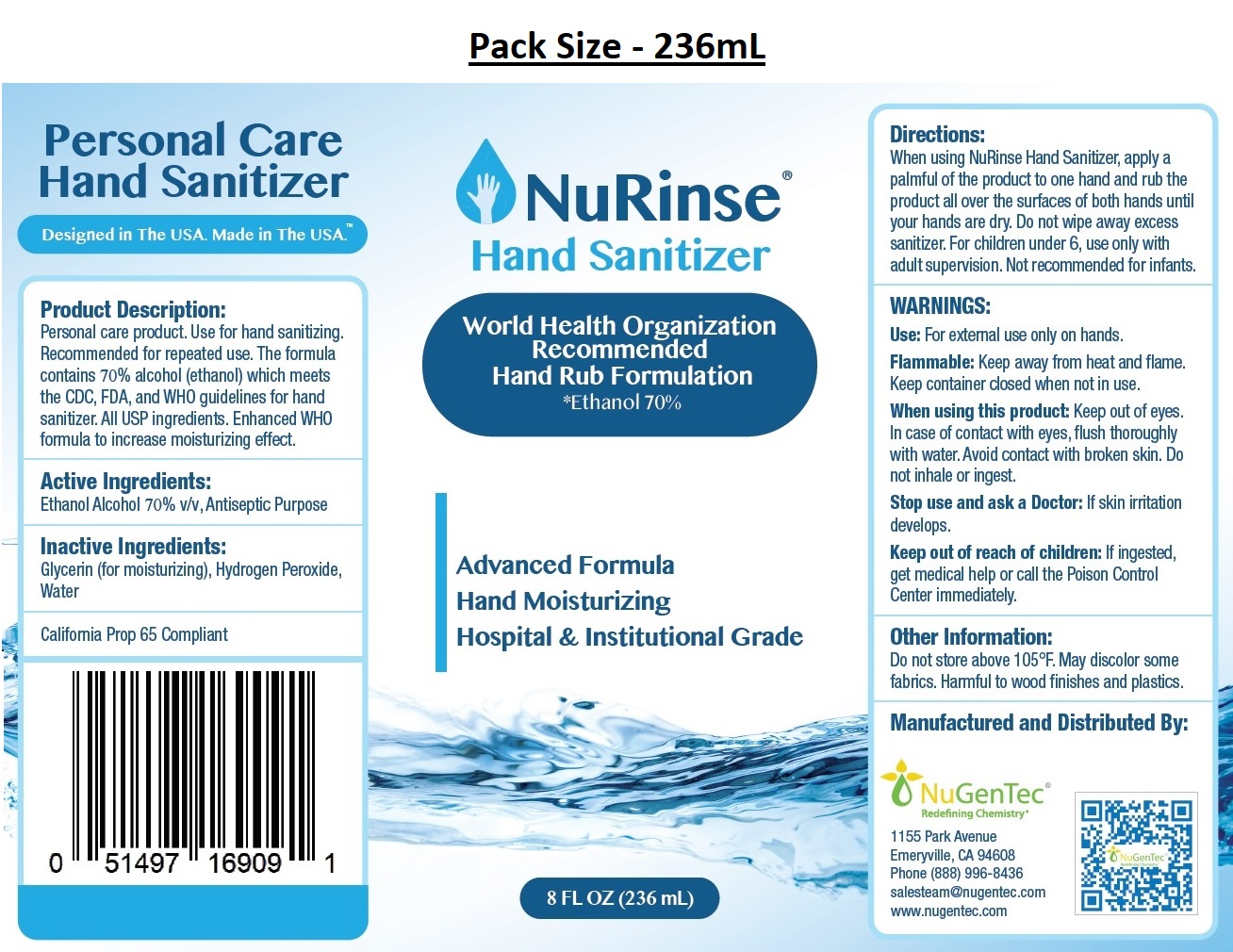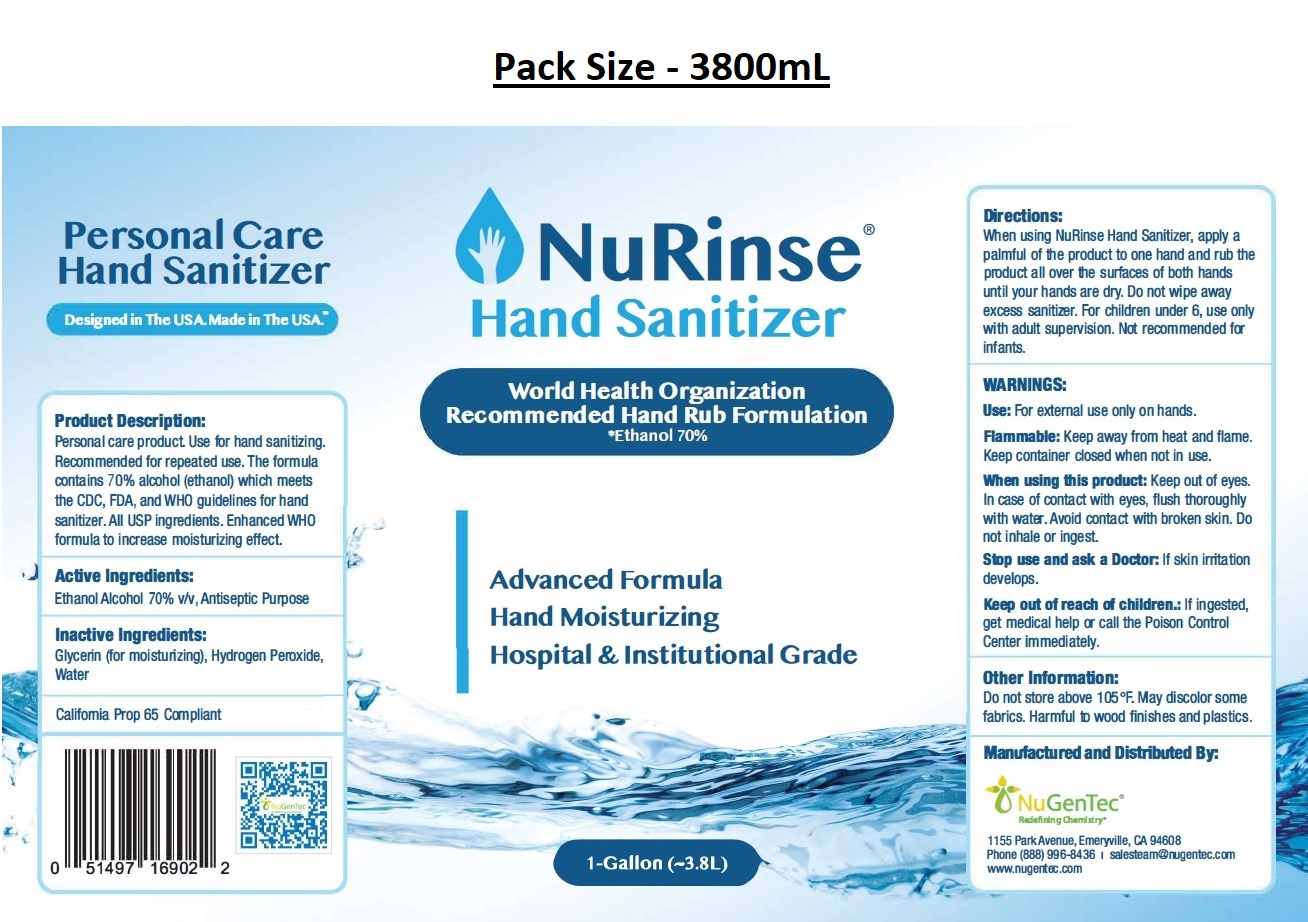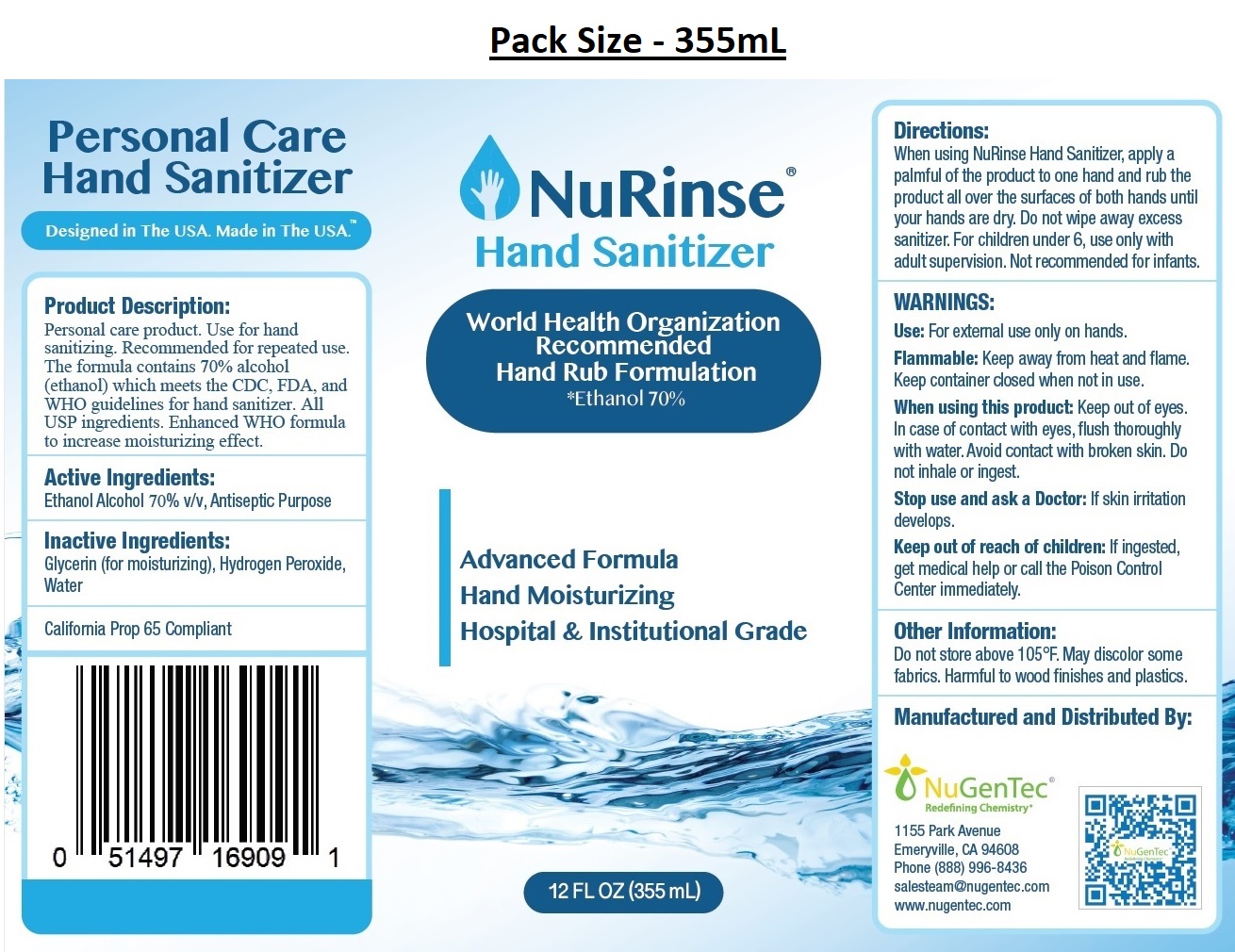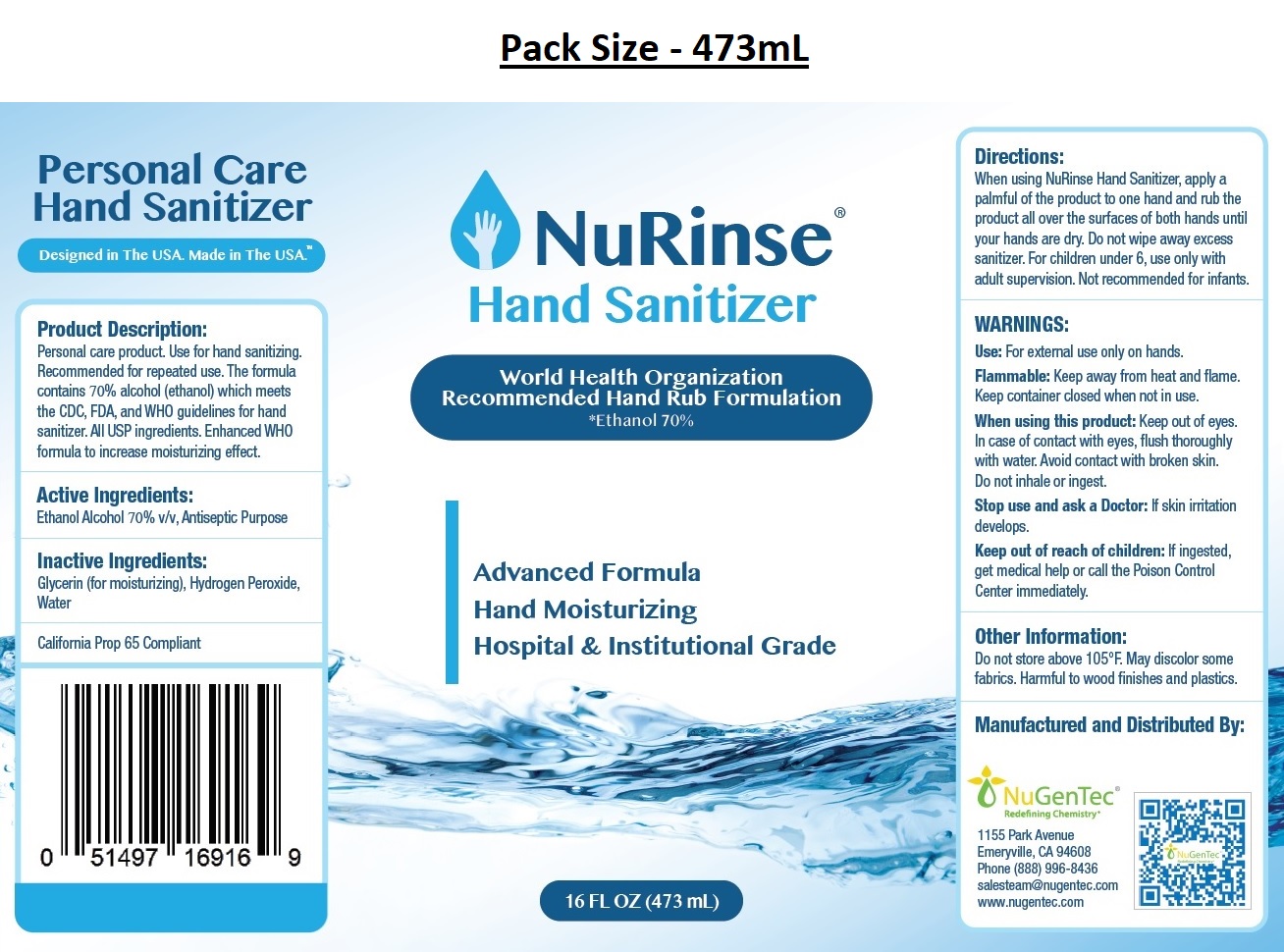 DRUG LABEL: NuRinse Hand Sanitizer
NDC: 77368-070 | Form: LIQUID
Manufacturer: NuGenTec
Category: otc | Type: HUMAN OTC DRUG LABEL
Date: 20200903

ACTIVE INGREDIENTS: ALCOHOL 70 mL/100 mL
INACTIVE INGREDIENTS: GLYCERIN; HYDROGEN PEROXIDE; WATER

NuRinse® Hand Sanitizer

Active Ingredients:

Ethanol Alcohol 70% v/v,

Purpose: Antiseptic

INDICATIONS AND USAGE

Use: For external use only on hands.

Inactive Ingredients:

Glycerin (for moisturizing), Hydrogen Peroxide, Water

Directions:

When using NuRinse Hand Sanitizer, apply a palmful of the product to one hand and rub the product all over the surfaces of both hands until your hands are dry. Do not wipe away excess sanitizer. For children under 6, use only with adult supervision. Not recommended for infants.

WARNINGS:

Flammable: Keep away from heat and flame. Keep container closed when not in use.
When using this product: Keep out of eyes. In case of contact with eyes, flush thoroughly with water. Avoid contact with broken skin. Do not inhale or ingest.
Stop use and ask a Doctor: If skin irritation develops.

Keep out of reach of children: If ingested, get medical help or call the Poison Control Center immediately.

Other Information:

Do not store above 105°F. May discolor some fabrics. Harmful to wood finishes and plastics.

World Health Organization Recommended Hand Rub Formulation
*Ethanol 70%

Advanced Formula
Hand Moisturizing
Hospital & Institutional Grade

Personal Care
Hand Sanitizer
Designed in The USA. Made in The USA.™

Product Description:
Personal care product. Use for hand sanitizing. Recommended for repeated use. The formula contains 70% alcohol (ethanol) which meets the CDC, FDA, and WHO guidelines for hand sanitizer. All USP ingredients. Enhanced WHO formula to increase moisturizing effect.

California Prop 65 Compliant

Manufactured and Distributed By:

NuGenTec®

Redefining Chemistry

1155 Park Avenue
Emeryville, CA 94608
Phone (888) 996-8436
salesteam@nugentec.com
www.nugentec.com